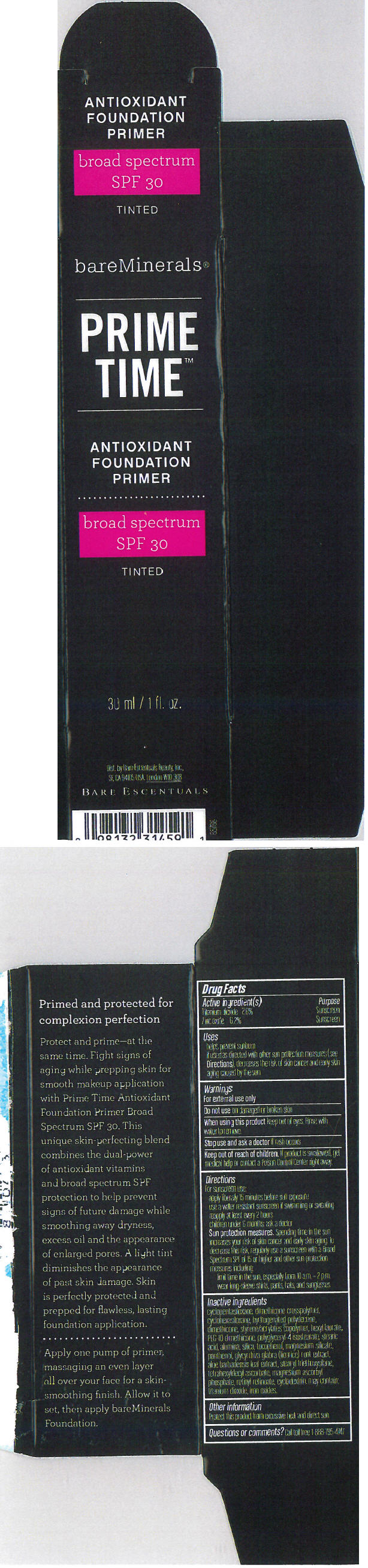 DRUG LABEL: Antioxidant Primer
NDC: 98132-184 | Form: CREAM
Manufacturer: Bare Escentuals Beauty Inc.
Category: otc | Type: HUMAN OTC DRUG LABEL
Date: 20130304

ACTIVE INGREDIENTS: Titanium Dioxide 26 mg/1 mL; Zinc Oxide 62 mg/1 mL
INACTIVE INGREDIENTS: CYCLOMETHICONE 5; DIMETHICONE; HEXYL LAURATE; PEG-10 DIMETHICONE (600 CST); POLYGLYCERYL-4 ISOSTEARATE; STEARIC ACID; ALUMINUM OXIDE; SILICON DIOXIDE; TOCOPHEROL; MAGNESIUM SILICATE; PANTHENOL; GLYCYRRHIZA GLABRA; ALOE VERA LEAF; STEARYL TRIETHOXYSILANE; TETRAHEXYLDECYL ASCORBATE; MAGNESIUM ASCORBYL PHOSPHATE; RETINYL RETINOATE; FERRIC OXIDE RED

Antioxidant Primer

Drug Facts

ACTIVE INGREDIENT

Active Ingredients | Purpose
Titanium Dioxide 2.6% | Sunscreen
Zinc oxide 6.2% | Sunscreen

Uses

Helps prevent sunburn. If used as directed with other sun protection measures (see Directions), decreases the risk of skin cancer and early skin aging caused by the sun.

Warnings

For external use only

Do not use on damaged or broken skin.

When using this product: Keep out of Eyes ; Rinse with water to remove

Stop use and ask a doctor if rash occurs.

Keep out of reach of children. If swallowed, get medical help or contact a Poison Control Center right away.

Directions

For sunscreen use:

Apply liberally 15 minutes before sun exposure

Use a water resistant sunscreen if swimming or sweating

Reapply at least every 2 hours

Children under 6 months, ask a doctor.

Sun protection measures. Spending time in the sun increases your risk of skin cancer and early skin aging. To decrease this risk, regularly use a sunscreen with a Broad Spectrum SPF of 15 or higher and other sun protection measures including: limit time in the sun, especially from 10am to 2 pm, wear long-sleeve shirts, pants, hats, and sunglasses.

Inactive Ingredients

Cyclopentasiloxane, dimethicone crosspolymer, dimethicone, styrene/acrylates copolymer, hexyl laurate, PEG 10 dimethicone, polyglycerol 4 isostearate, stearic acid, alumina, silica, topcopherol, magnesium silicate, panthenol, glycyrrhiza glaba (licorice) root extract, aloe bardenesis leaf extract, stearyl triethoxysilane, tetrahexyldecyl ascorbate, magnesium ascorbyl phosphate, retinyl retinoate, cyclodextrin. May contain: titanium dioxide and iron oxides.

Other information

Protect this product from excessive heat and direct sun

Questions or comments?

Call toll free 1-888-795-4747

Bare Escentuals
MADE IN USA
Distr. By Bare Escentuals Beauty Inc., San Francisco CA 94104 USA
London W10 3QB

PRINCIPAL DISPLAY PANEL - 30 ml Bottle Carton

bareMinerals®

PRIME
TIME™

ANTIOXIDANT
FOUNDATION
PRIMER

broad spectrum
SPF 30

TINTED

30 ml / 1 fl. oz.